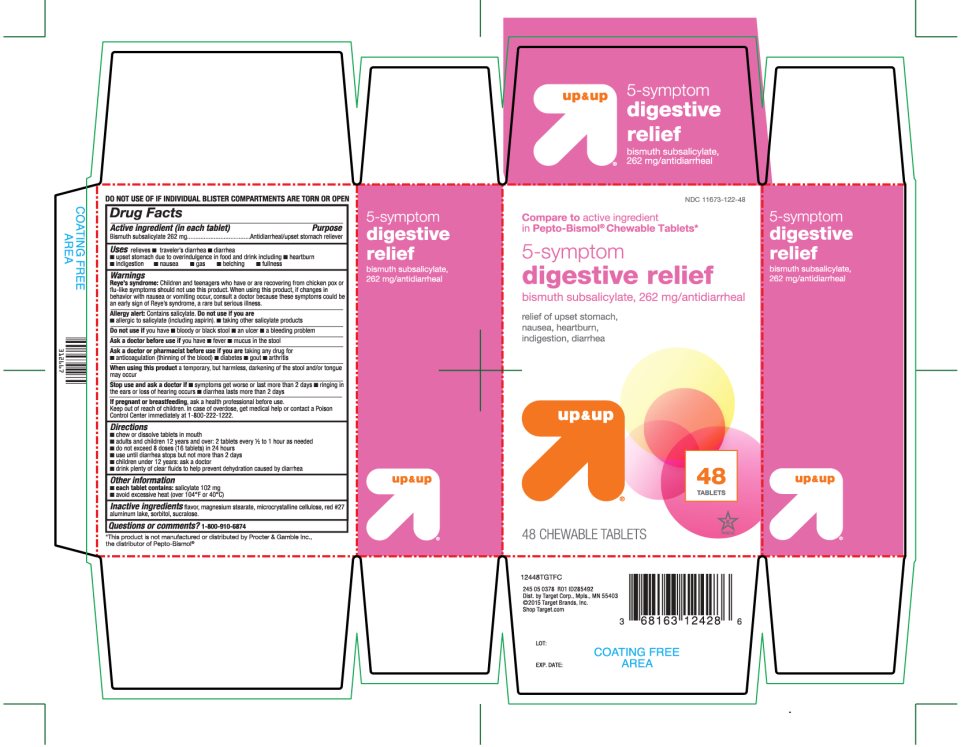 DRUG LABEL: up and up 5-symptom digestive relief
NDC: 11673-122 | Form: TABLET
Manufacturer: Target Corporation
Category: otc | Type: HUMAN OTC DRUG LABEL
Date: 20251104

ACTIVE INGREDIENTS: BISMUTH SUBSALICYLATE 262 mg/1 1
INACTIVE INGREDIENTS: MAGNESIUM STEARATE; MICROCRYSTALLINE CELLULOSE; D&C RED NO. 27; SORBITOL; SUCRALOSE

Up & Up 5-Symptoms Digestive Relief 48 Chewable Tablets

Drug Facts

Active ingredient (in each tablet)

Bismuth subsalicylate 262 mg

Purpose

Anti-diarrheal/Upset stomach reliever

Uses

relieves

- traveler’s diarrhea
- diarrhea
- upset stomach due to overindulgence in food and drink including
- heartburn
- indigestion
- nausea
- gas
- belching
- fullness

Warnings

Reye's syndrome

Children and teenagers who have or are recovering from chicken pox or flu-like symptoms should not use this product. When using this product, if changes in behavior with nausea and vomiting occur, consult a doctor because these symptoms could be an early sign of Reye's syndrome, a rare but serious illness.

Allergy alert:

Contains salicylate. Do not take if you are

- allergic to salicylates (including aspirin)
- taking other salicylate products

Do not use ifyou have

- bloody or black stool
- an ulcer
- a bleeding problem

Ask a doctor before use if you have

- fever
- mucus in the stool

Ask a doctor before use if you are taking any drug for

- anticoagulation (thinning of the blood)
- diabetes
- gout
- arthritis

WHEN USING

When using this producta temporary, but harmless, darkening of the stool and/or tongue may occur.

Stop use and ask a doctor if

- symptoms get worse or last more than 2 days
- ringing in the ears occurs or loss of hearing occurs
- diarrhea lasts more than 2 days

PREGNANCY OR BREAST FEEDING

If pregnant or breast feeding,ask a health professional before use.

Keep out of reach of children. In case of overdose, get medical help or contact a Poison Control Center immediately.1-800-222-1222.

Directions

- chew or dissolve tablets in mouth
- adults and children 12 years and older:2 caplets every 1/2 to 1 hour as needed
- do not exceed 8 doses (16 caplets) in 24 hours
- use until diarrhea stops but not more than 2 days
- children under 12 years:ask a doctor
- drink plenty of clear fluids to help prevent dehydration caused by diarrhea

Other information

- each tablets contains:salicylate 102 mg
- avoid excessive heat (over 104°F or 40°C)

Inactive ingredients

Flavor, magnesium stearate, microcrystalline cellulose, red# 27 aluminum lake, sorbitol, sucralose.

PRINCIPAL DISPLAY PANEL

NDC 11673-122-48

Compare toactive ingredient in Pepto-Bismol® Chewable Tablets*

5- symptom digestive relief

Bismuth subsalicylate, 262 mg/antidiarrheal

relief of upset stomach, nausea, heartburn, indigestion, diarrhea

48 TABLETS

K PARAVE

48 CHEWABLE TABLETS

TAMPER EVIDENT: DO NOT USE IF INDIVIDUAL BLISTER COMPARTMENTS ARE TORN OR OPEN

245 05 0378 R01 ID285492

Dist.by Target Corp., Mpls, MN 55403

©2015 Target Brands, Inc.

Shop Target.com

*This product is not manufactured or distributed by Procter & Gamble Inc., the distributor of PEPTO-BISMOL®